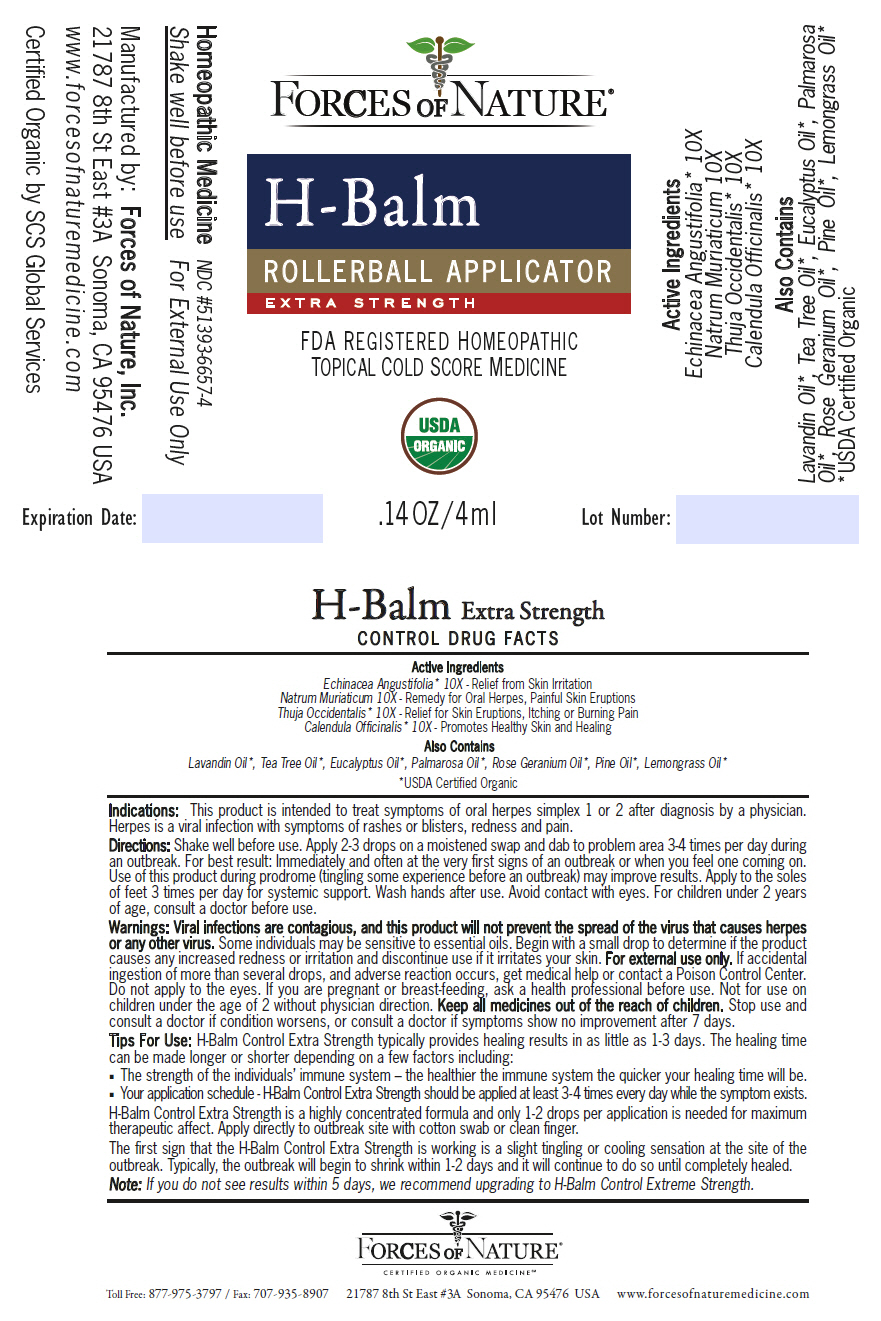 DRUG LABEL: H-Balm Control 
NDC: 51393-6657 | Form: SOLUTION/ DROPS
Manufacturer: Forces of Nature
Category: homeopathic | Type: HUMAN OTC DRUG LABEL
Date: 20200424

ACTIVE INGREDIENTS: CALENDULA OFFICINALIS FLOWERING TOP 10 [hp_X]/1000 mL; ECHINACEA, UNSPECIFIED 10 [hp_X]/1000 mL; SODIUM CHLORIDE 10 [hp_X]/1000 mL; THUJA OCCIDENTALIS LEAFY TWIG 10 [hp_X]/1000 mL
INACTIVE INGREDIENTS: Lavandin Oil; Tea Tree Oil; GERANIUM OIL, ALGERIAN TYPE; EAST INDIAN LEMONGRASS OIL; PALMAROSA OIL; EUCALYPTUS OIL; WHITE PINE OIL

H-Balm Control
Extra Strength

DRUG FACTS

Active Ingredients

Echinacea Angustifolia [USDA Certified Organic] 10X - Relief from Skin Irritation

Natrum Muriaticum 10X - Remedy for Oral Herpes, Painful Skin Eruptions

Thuja Occidentalis 10X - Relief for Skin Eruptions, Itching or Burning Pain

Calendula Officinalis 10X - Promotes Healthy Skin and Healing

Also Contains

Lavandin Oil, Tea Tree Oil, Eucalyptus Oil, Palmarosa Oil, Rose Geranium Oil, Pine Oil, Lemongrass Oil

Indications

PURPOSE

This product is intended to treat symptoms of oral herpes simplex 1 or 2 after diagnosis by a physician. Herpes is a viral infection with symptoms of rashes or blisters, redness and pain.

Directions

Shake well before use. Apply 2-3 drops on a moistened swap and dab to problem area 3-4 times per day during an outbreak. For best result: Immediately and often at the very first signs of an outbreak or when you feel one coming on. Use of this product during prodrome (tingling some experience before an outbreak) may improve results. Apply to the soles of feet 3 times per day for systemic support. Wash hands after use. Avoid contact with eyes. For children under 2 years of age, consult a doctor before use.

Warnings

Viral infections are contagious, and this product will not prevent the spread of the virus that causes herpes or any other virus. Some individuals may be sensitive to essential oils. Begin with a small drop to determine if the product causes any increased redness or irritation and discontinue use if it irritates your skin. For external use only. If accidental ingestion of more than several drops, and adverse reaction occurs, get medical help or contact a Poison Control Center. Do not apply to the eyes. If you are pregnant or breast-feeding, ask a health professional before use. Not for use on children under the age of 2 without physician direction.

KEEP OUT OF REACH OF CHILDREN

Keep all medicines out of the reach of children.

Stop use and consult a doctor if condition worsens, or consult a doctor if symptoms show no improvement after 7 days.

Tips For Use

H-Balm Control Extra Strength typically provides healing results in as little as 1-3 days. The healing time can be made longer or shorter depending on a few factors including:

- The strength of the individuals' immune system – the healthier the immune system the quicker your healing time will be.
- Your application schedule - H-Balm Control Extra Strength should be applied at least 3-4 times every day while the symptom exists.

H-Balm Control Extra Strength is a highly concentrated formula and only 1-2 drops per application is needed for maximum therapeutic affect. Apply directly to outbreak site with cotton swab or clean finger.

The first sign that the H-Balm Control Extra Strength is working is a slight tingling or cooling sensation at the site of the outbreak. Typically, the outbreak will begin to shrink within 1-2 days and it will continue to do so until completely healed.

Note: If you do not see results within 5 days, we recommend upgrading to H-Balm Control Extreme Strength.

Manufactured by: Forces of Nature, Inc.
21787 8th St East #3A Sonoma, CA 95476 USA

PRINCIPAL DISPLAY PANEL - 4 ml Bottle Label

FORCES OF NATURE®

H-Balm
ROLLERBALL APPLICATOR
EXTRA STRENGTH

FDA REGISTERED HOMEOPATHIC
TOPICAL COLD SCORE MEDICINE

USDA
ORGANIC

.14 OZ/4 ml